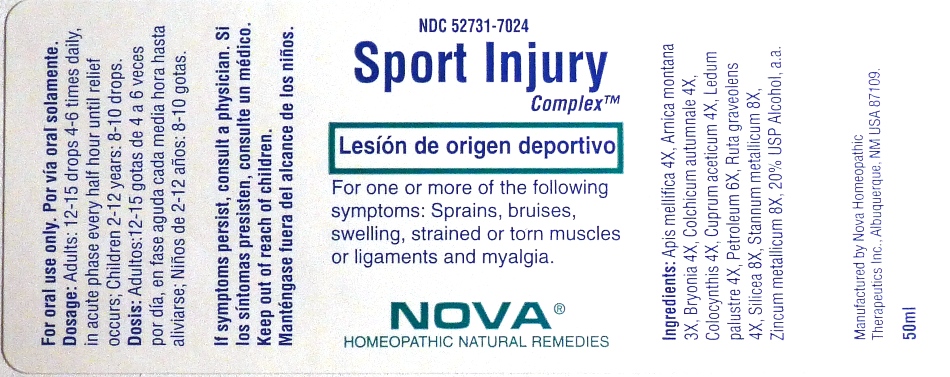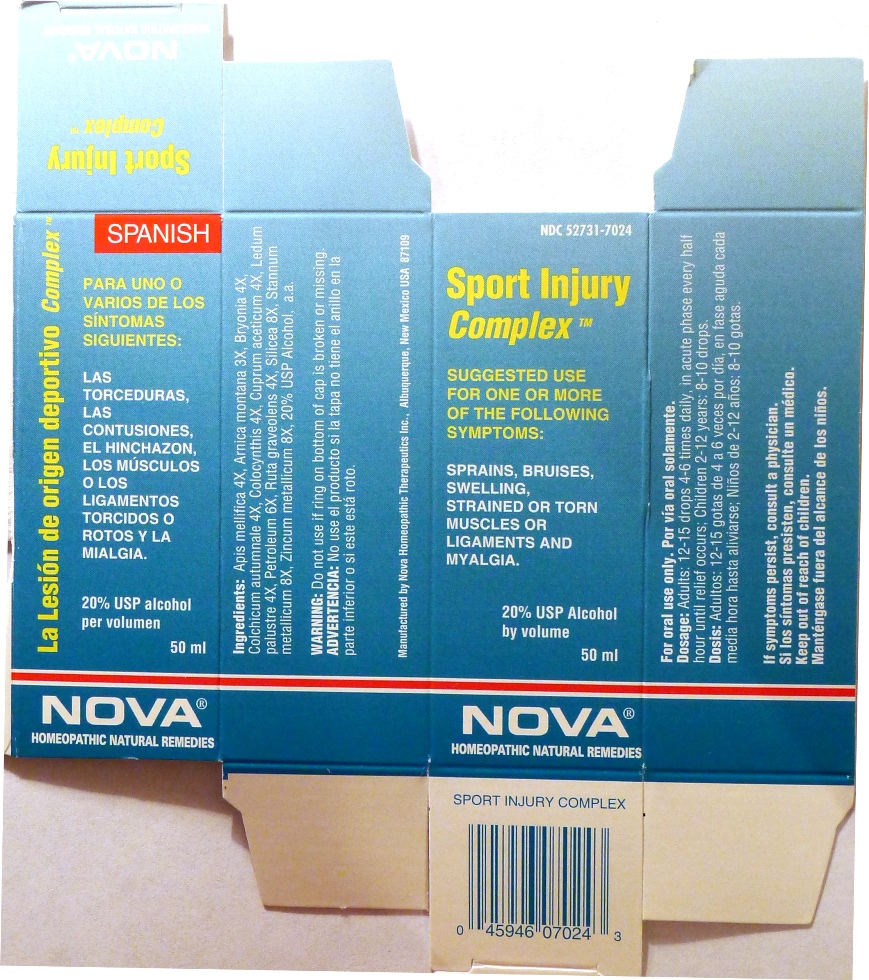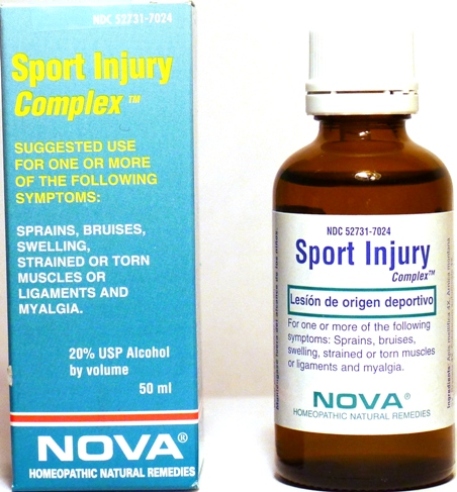 DRUG LABEL: Sport Injury Complex
NDC: 52731-7024 | Form: LIQUID
Manufacturer: Nova Homeopathic Therapeutics, Inc.
Category: homeopathic | Type: HUMAN OTC DRUG LABEL
Date: 20110601

ACTIVE INGREDIENTS: APIS MELLIFERA 4 [hp_X]/1 mL; ARNICA MONTANA 3 [hp_X]/1 mL; BRYONIA ALBA ROOT 4 [hp_X]/1 mL; COLCHICUM AUTUMNALE BULB 4 [hp_X]/1 mL; CITRULLUS COLOCYNTHIS FRUIT PULP 4 [hp_X]/1 mL; CUPRIC ACETATE 4 [hp_X]/1 mL; LEDUM PALUSTRE TWIG 4 [hp_X]/1 mL; LIQUID PETROLEUM 6 [hp_X]/1 mL; RUTA GRAVEOLENS FLOWERING TOP 4 [hp_X]/1 mL; SILICON DIOXIDE 8 [hp_X]/1 mL; TIN 8 [hp_X]/1 mL; ZINC 8 [hp_X]/1 mL
INACTIVE INGREDIENTS: ALCOHOL

Sport Injury Complex

Purpose:

Suggested use for one or more of the following symptoms:

Sprains, bruises, swelling, strained or torn muscles or ligaments and myalgia.

Usage and Dosage:

For oral use only.

DOSAGE AND ADMINISTRATION

Adults:
In Acute Phase:
12-15 drops, every half hour until relief occurs
When Relief Occurs:
12-15 drops, 4-6 times per day
Children 2-12 years:
8-10 drops, 4-6 times per day

Warnings:

Keep out of reach of children.

WARNINGS

If symptoms persist, consult a physician.
Do not use if ring on bottom of cap is broken or missing.

Active Ingredients:

Apis mellifica 4X, Arnica montana 3X, Bryonia 4X, Colchicum autumnale 4X, Colocynthis 4X, Cuprum aceticum 4X, Ledum paustre 4X, Petroleum 6X, Ruta graveolens 4X, Silicea 8X, Stannum metallicum 8X, Zincum metallicum 8X

Inactive Ingredients:

Alcohol, 20% USP

QUESTIONS

Manufactured by Nova Homeopathic Therapeutics Inc., Albuquerque, New Mexico USA 87109
1-800-225-8094

PACKAGE LABEL

Sport Injury Complex Product

Sport Injury Complex Bottle Label

Sport Injury Complex Box